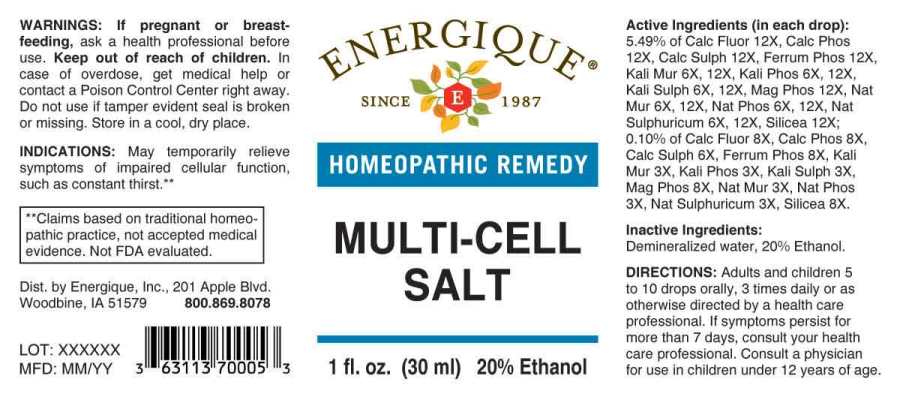 DRUG LABEL: Multi-Cell Salt
NDC: 44911-0160 | Form: LIQUID
Manufacturer: Energique, Inc.
Category: homeopathic | Type: HUMAN OTC DRUG LABEL
Date: 20241029

ACTIVE INGREDIENTS: POTASSIUM CHLORIDE 3 [hp_X]/1 mL; DIBASIC POTASSIUM PHOSPHATE 3 [hp_X]/1 mL; POTASSIUM SULFATE 3 [hp_X]/1 mL; SODIUM CHLORIDE 3 [hp_X]/1 mL; SODIUM PHOSPHATE, DIBASIC, HEPTAHYDRATE 3 [hp_X]/1 mL; SODIUM SULFATE 3 [hp_X]/1 mL; CALCIUM SULFATE ANHYDROUS 6 [hp_X]/1 mL; CALCIUM FLUORIDE 8 [hp_X]/1 mL; TRIBASIC CALCIUM PHOSPHATE 8 [hp_X]/1 mL; FERROSOFERRIC PHOSPHATE 8 [hp_X]/1 mL; MAGNESIUM PHOSPHATE, DIBASIC TRIHYDRATE 8 [hp_X]/1 mL; SILICON DIOXIDE 8 [hp_X]/1 mL
INACTIVE INGREDIENTS: WATER; ALCOHOL

DRUG FACTS:

ACTIVE INGREDIENTS:

(in each drop): 5.49% of Calcarea Fluorica 12X, Calcarea Phosphorica 12X, Calcarea Sulphurica 12X, Ferrum Phosphoricum 12X, Kali Muriaticum 6X, 12X, Kali Phosphoricum 6X, 12X, Kali Sulphuricum 6X, 12X, Magnesia Phosphorica 12X, Natrum Muriaticum 6X, 12X, Natrum Phosphoricum 6X, 12X, Natrum Sulphuricum 6X, 12X, Silicea 12X; 0.10% of Calcarea Fluorica 8X, Calcarea Phosphorica 8X, Calcarea Sulphurica 6X, Ferrum Phosphoricum 8X, Kali Muriaticum 3X, Kali Phosphoricum 3X, Kali Sulphuricum 3X, Magnesia Phosphorica 8X, Natrum Muriaticum 3X, Natrum Phosphoricum 3X, Natrum Sulphuricum 3X, Silicea 8X.

INDICATIONS:

May temporarily relieve symptoms of impaired cellular function, such as constant thirst.**

**Claims based on traditional homeopathic practice, not accepted medical evidence. Not FDA evaluated.

WARNINGS:

If pregnant or breast-feeding, ask a health professional before use.

Keep out of reach of children. In case of overdose, get medical help or contact a Poison Control Center right away.

Do not use if tamper evident seal is broken or missing. Store in a cool, dry place.

Keep out of reach of children. In case of overdose, get medical help or contact a Poison Control Center right away.

DIRECTIONS:

Adults and children 5 to 10 drops orally, 3 times daily or as otherwise directed by a health care professional. If symptoms persist for more than 7 days, consult your health care professional. Consult a physician for use in children under 12 years of age.

INDICATIONS:

May temporarily relieve symptoms of impaired cellular function, such as constant thirst.**

**Claims based on traditional homeopathic practice, not accepted medical evidence. Not FDA evaluated.

INACTIVE INGREDIENTS:

Demineralized water, 20% Ethanol.

QUESTIONS:

Dist. by Energique, Inc.

201 Apple Blvd

Woodbine, IA 51579 800.869.8078

PACKAGE LABEL DISPLAY:

ENERGIQUE

SINCE 1987

HOMEOPATHIC REMEDY

MULTI-CELL
SALT

1 fl. oz. (30 ml)